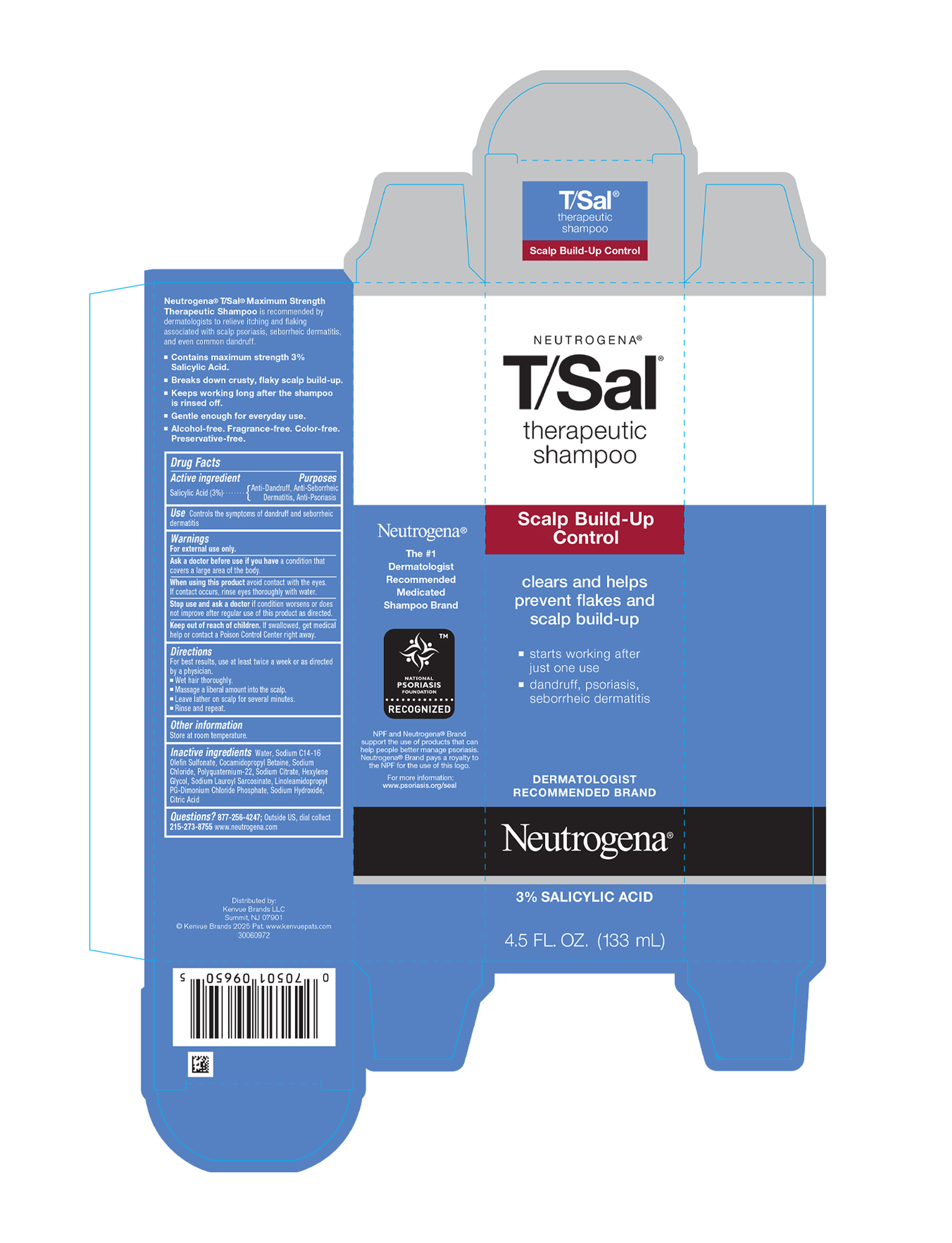 DRUG LABEL: Neutrogena T/Sal Therapeutic
NDC: 69968-0434 | Form: SHAMPOO
Manufacturer: Kenvue Brands LLC
Category: otc | Type: HUMAN OTC DRUG LABEL
Date: 20250605

ACTIVE INGREDIENTS: SALICYLIC ACID 30 mg/1 mL
INACTIVE INGREDIENTS: WATER; SODIUM C14-16 OLEFIN SULFONATE; COCAMIDOPROPYL BETAINE; SODIUM CHLORIDE; SODIUM CITRATE, UNSPECIFIED FORM; SODIUM LAUROYL SARCOSINATE; HEXYLENE GLYCOL; LINOLEAMIDOPROPYL PROPYLENE GLYCOL-DIMONIUM CHLORIDE PHOSPHATE; SODIUM HYDROXIDE; CITRIC ACID MONOHYDRATE

NEUTROGENA® T/Sal® therapeutic shampoo

Drug Facts

Active ingredient

Salicylic Acid (3%)

Purposes

Anti-Dandruff, Anti-Seborrheic Dermatitis, Anti-Psoriasis

Use

Controls the symptoms of dandruff and seborrheic dermatitis

Warnings

For external use only.

Ask a doctor before use if you have a condition that covers a large area of the body.

When using this product avoid contact with the eyes. If contact occurs, rinse eyes thoroughly with water.

Stop use and ask a doctor if condition worsens or does not improve after regular use of this product as directed.

Keep out of reach of children. If swallowed, get medical help or contact a Poison Control Center right away.

Directions

For best results, use at least twice a week or as directed by a physician .

- Wet hair thoroughly.
- Massage a liberal amount into the scalp.
- Leave lather on scalp for several minutes.
- Rinse and repeat.

Other information

Store at room temperature.

Inactive ingredients

Water, Sodium C14-16 Olefin Sulfonate, Cocamidopropyl Betaine, Sodium Chloride, Polyquaternium-22, Sodium Citrate, Hexylene Glycol, Sodium Lauroyl Sarcosinate, Linoleamidopropyl PG-Dimonium Chloride Phosphate, Sodium Hydroxide, Citric Acid

Questions?

877-256-4247; Outside US, dial collect 215-273-8755 www.neutrogena.com

Distributed by:
Kenvue Brands LLC
Summit, NJ 07901

PRINCIPAL DISPLAY PANEL - 133 mL Bottle Carton

NEUTROGENA®
T/Sal®
therapeutic
shampoo

Scalp Build-Up
Control

clears and helps
prevent flakes and
scalp build-up

- starts working after
  just one use
- dandruff, psoriasis,
  seborrheic dermatitis

DERMATOLOGIST
RECOMMENDED BRAND
Neutrogena®
3% SALICYLIC ACID
4.5 FL. OZ. (133 mL)